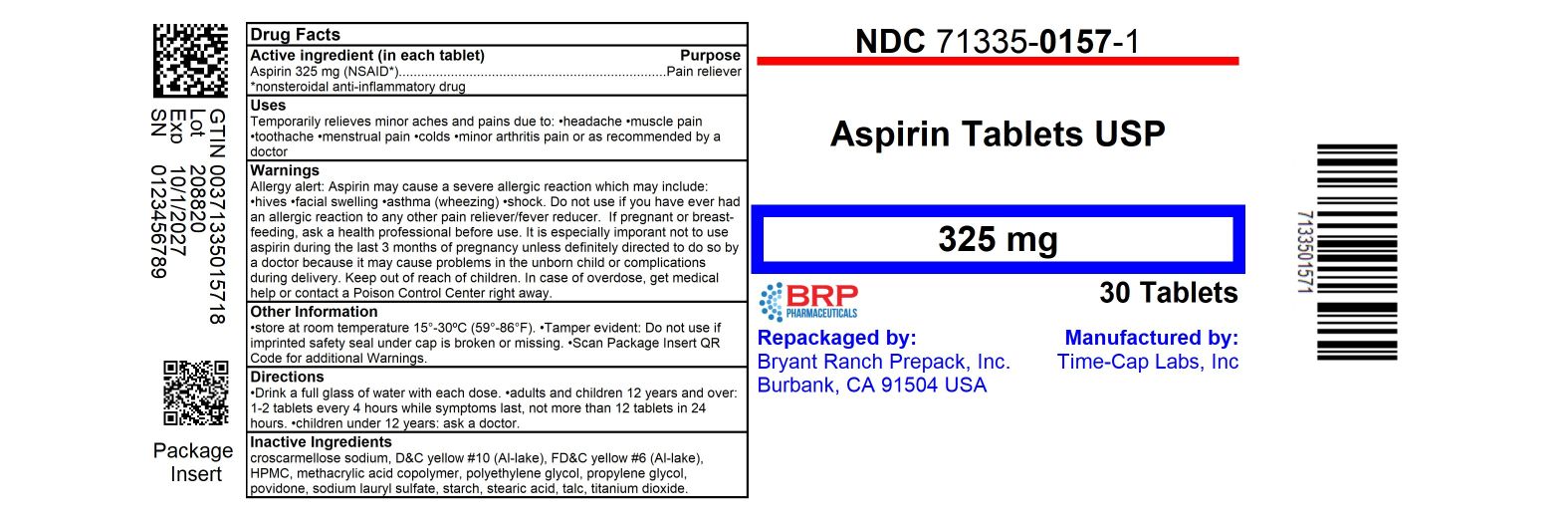 DRUG LABEL: Enteric Coated Aspirin
NDC: 71335-0157 | Form: TABLET, DELAYED RELEASE
Manufacturer: Bryant Ranch Prepack
Category: otc | Type: HUMAN OTC DRUG LABEL
Date: 20251001

ACTIVE INGREDIENTS: ASPIRIN 325 mg/1 1
INACTIVE INGREDIENTS: STARCH, CORN; CROSCARMELLOSE SODIUM; D&C YELLOW NO. 10 ALUMINUM LAKE; FD&C YELLOW NO. 6; METHACRYLIC ACID - ETHYL ACRYLATE COPOLYMER (1:1) TYPE A; MICROCRYSTALLINE CELLULOSE; MINERAL OIL; POLYSORBATE 80; DIMETHICONE; SILICON DIOXIDE; SODIUM HYDROXIDE; SODIUM LAURYL SULFATE; TALC; TITANIUM DIOXIDE; TRIETHYL CITRATE; HYPROMELLOSE, UNSPECIFIED

331R Timely 49483-331 Aspirin 325mg Delayed Release Tablets

Active ingredient (in each tablet)
Aspirin 325 mg (NSAID*) *nonsteroidal anti-inflammatory drug

Purpose
Pain reliever

Uses
temporarily relieves minor aches and pains due to:

- headache
- muscle pain
- toothache
- menstrual pain
- colds
- minor arthritis pain

or as recommended by a doctor

Warnings
Reye’s syndrome: Children and teenagers who have or are recovering from chicken pox or flu-like symptoms should not use this product. When using this product, if changes in behavior with nausea and vomiting occur, consult a doctor because these symptoms could be an early sign of Reye's
syndrome, a rare but serious illness.
Allergy alert: Aspirin may cause a severe allergic reaction, which may include:

- hives
- facial swelling
- shock
- asthma (wheezing)

Stomach bleeding warning: This product contains an NSAID, which may cause severe stomach bleeding. The chance is higher if you:

- are age 60 or older
- have had stomach ulcers or bleeding problems
- take a blood thinning (anticoagulant) or steroid drug
- take other drugs containing prescription or nonprescription NSAIDs (aspirin, ibuprofen, naproxen, or others)
- have 3 or more alcoholic drinks every day while using this product
- take more or for a longer time than directed

Do not use

- if you are allergic to aspirin or any other pain reliever/fever reducer

Ask a doctor before use if

- stomach bleeding warning applies to you
- you have a history of stomach problems, such as heartburn
- you have high blood pressure, heart disease, liver cirrhosis, or kidney disease
- you are taking a diuretic
- you have asthma

Ask a doctor or pharmacist before use if you are

- taking a prescription drug for diabetes, gout, or arthritis

Stop use and ask a doctor if

- an allergic reaction occurs. Seek medical help right away.
- you experience any of the following signs of stomach bleeding:

feel faint
have bloody or black stools
vomit blood
have stomach pain that does not get better

- pain gets worse or lasts more than 10 days
- redness or swelling is present
- new symptoms occur
- ringing in the ears or a loss of hearing occurs

These could be signs of a serious condition.

PREGNANCY OR BREAST FEEDING

If pregnant or breast-feeding, ask a health professional before use. It is especially important not to use aspirin during the last 3 months of pregnancy unless definitely directed to do so by a doctor because it may cause problems in the unborn child or complications during delivery.

Keep out of reach of children. In case of accidental overdose, get medical help or contact a Poison Control Center (1-800-222-1222) right away.

Directions

- drink a full glass of water with each dose
- adults and children 12 years and over: take 1 to 2 tablets every 4 hours while symptoms last. Do not take more than 12 tablets in 24 hours unless directed by a doctor
- children under 12 years: consult a doctor

Other information

- each tablet contains: sodium 1 mg (VERY LOW SODIUM)
- store at 25°C (77°F) excursions permitted between 15°-30°C (59°-86°F)
- use by expiration date on package

INACTIVE INGREDIENT

Inactive ingredients corn starch, croscarmellose sodium, D&C yellow #10 aluminum lake, FD&C yellow #6 aluminum lake, hypromellose, methacrylic acid and ethyl acrylate copolymer, microcrystalline cellulose, mineral oil, polysorbate 80, simethicone, sodium hydroxide, sodium lauryl sulfate, talc, titanium dioxide, triethyl citrate

Questions or comments? call 1-877-290-4008

HOW SUPPLIED

Aspirin 325 mg (NSAID*) *Non-Steroidal Anti-Inflammatory Drug

- NDC 71335-0157-1: 30 Tablets in a BOTTLE
- NDC 71335-0157-2: 60 Tablets in a BOTTLE
- NDC 71335-0157-3: 100 Tablets in a BOTTLE
- NDC 71335-0157-4: 90 Tablets in a BOTTLE
- NDC 71335-0157-5: 20 Tablets in a BOTTLE
- NDC 71335-0157-6: 45 Tablets in a BOTTLE
- NDC 71335-0157-7: 120 Tablets in a BOTTLE
- NDC 71335-0157-8: 7 Tablets in a BOTTLE

store at 25°C (77°F) excursions permitted between 15°-30°C (59°-86°F)

Repackaged/Relabeled by:
Bryant Ranch Prepack, Inc.
Burbank, CA 91504

PACKAGE LABEL

Aspirin 325mg Tablets